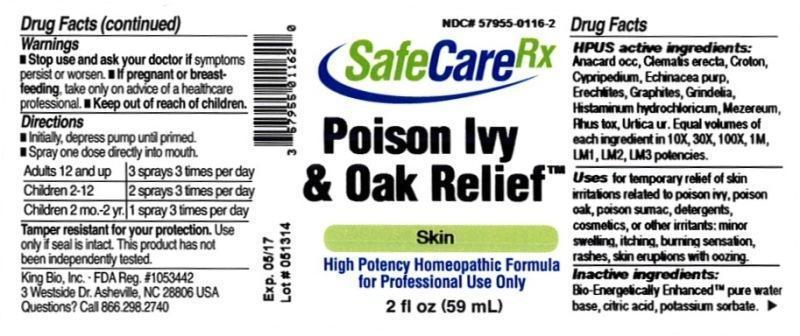 DRUG LABEL: Poison Ivy and Oak Relief
NDC: 57955-0116 | Form: LIQUID
Manufacturer: King Bio Inc.
Category: homeopathic | Type: HUMAN OTC DRUG LABEL
Date: 20140528

ACTIVE INGREDIENTS: ANACARDIUM OCCIDENTALE FRUIT 10 [hp_X]/59 mL; CLEMATIS RECTA FLOWERING TOP 10 [hp_X]/59 mL; CROTON TIGLIUM SEED 10 [hp_X]/59 mL; CYPRIPEDIUM PARVIFOLUM ROOT 10 [hp_X]/59 mL; ECHINACEA PURPUREA 10 [hp_X]/59 mL; ERECHTITES HIERACIIFOLIUS 10 [hp_X]/59 mL; GRAPHITE 10 [hp_X]/59 mL; GRINDELIA HIRSUTULA WHOLE 10 [hp_X]/59 mL; HISTAMINE DIHYDROCHLORIDE 10 [hp_X]/59 mL; DAPHNE MEZEREUM BARK 10 [hp_X]/59 mL; TOXICODENDRON PUBESCENS LEAF 10 [hp_X]/59 mL; URTICA URENS 10 [hp_X]/59 mL
INACTIVE INGREDIENTS: WATER; CITRIC ACID MONOHYDRATE; POTASSIUM SORBATE

Poison Ivy and Oak Relief™

ACTIVE INGREDIENT

Drug Facts__________________________________________________________________________________________________________

HPUS active ingredients: Anacardium occidentale, Clematis erecta, Croton tiglium, Cypripedium pubescens, Echinacea purpurea, Erechtites hieracifolia, Graphites, Grindelia, Histaminum hydrochloricum, Mezereum, Rhus toxicodendron, Urtica urens. Equal volumes of each ingredient in 10X, 30X, 100X, 1M, LM1, LM2, LM3, potencies.

INDICATIONS AND USAGE

Uses for temporary relief of skin irritations related to poison ivy, poison oak, poison sumac, detergents, cosmetics, or other irritants: minor swelling, itching, burning sensation, rashes, skin eruptions with oozing.

Inactive Ingredients:

Bio-Energetically Enhanced™ pure water, citric acid and potassium sorbate.

Warnings

- Stop use and ask your doctor if symptoms persist or worsen.
- If pregnant or breast-feeding, take only on advice of a healthcare professional.

- Keep out of reach of children.

Directions

- Initially, depress pump until primed.
- Spray one dose directly into mouth.
- Adults 12 and up: 3 sprays 3 times per day.
- Children 2-12: 2 sprays 3 times per day.
- Children 2 mo-2yr: 1 spray 3 times per day.

OTHER SAFETY INFORMATION

Tamper resistant for your protection. Use only if seal is intact. This product has not been independently tested.

PURPOSE

Uses for temporary relief of skin irritations related to poison ivy, poison oak, poison sumac, detergents, cosmetics, or other irritants:

- minor swelling
- itching
- burning sensation
- rashes
- skin eruptions with oozing